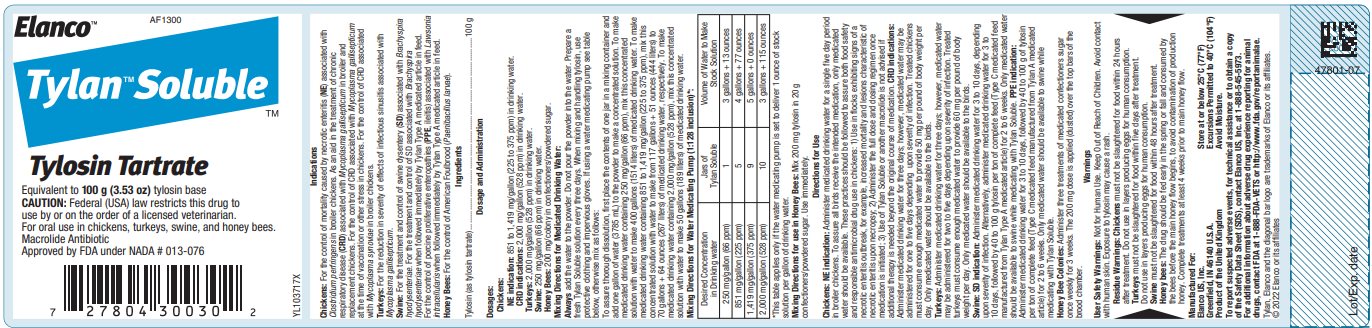 DRUG LABEL: Tylan Soluble
NDC: 58198-1300 | Form: POWDER
Manufacturer: Elanco US Inc.
Category: animal | Type: PRESCRIPTION ANIMAL DRUG LABEL
Date: 20251121

ACTIVE INGREDIENTS: tylosin tartrate 100 g/3785 mL

Elanco™

AF1300

Tylan™ SolubleTM

Tylosin Tartrate

Equivalent to 100 g (3.53 oz) tylosin base

CAUTION: Federal (USA) law restricts this drug to use by or on the order of a licensed veterinarian.

For oral use in chickens, turkeys, swine, and honey bees.

Macrolide Antibiotic

Approved by FDA under NADA # 013-076

Indications

Chickens: For the control of mortality caused by necrotic enteritis (NE) associated with Clostridium perfringens in broiler chickens. As an aid in the treatment of chronic respiratory disease (CRD) associated with Mycoplasma gallisepticum in broiler and replacement chickens. For the control of CRD associated with Mycoplasma gallisepticum at the time of vaccination or other stress in chickens. For the control of CRD associated with Mycoplasma synoviae in broiler chickens.

Turkeys: For the reduction in severity of effects of infectious sinusitis associated with Mycoplasma gallisepticum.

Swine: For the treatment and control of swine dysentery (SD) associated with Brachyspira hyodysenteriae. For the treatment and control of SD associated with Brachyspira hyodysenteriae when followed immediately by Tylan Type A medicated article in feed. For the control of porcine proliferative enteropathies (PPE, ileitis) associated with Lawsonia intracellularis when followed immediately by Tylan Type A medicated article in feed.

Honey Bees: For the control of American Foulbrood (Paenibacillus larvae).

Ingredients

Tylosin (as tylosin tartrate).........................................................................................100 g

Dosage and Administration

Dosages:

Chickens:

NE indication: 851 to 1,419 mg/gallon (225 to 375 ppm) in drinking water.

CRD indications: 2,000 mg/gallon (528 ppm) in drinking water.

Turkeys: 2,000 mg/gallon (528 ppm) in drinking water.

Swine: 250 mg/gallon (66 ppm) in drinking water.

Honey Bees: 200 mg/colony in confectioners/powdered sugar.

Mixing Directions for Medicated Drinking Water:

Always add the water to the powder. Do not pour the powder into the water. Prepare a fresh Tylan Soluble solution every three days. When mixing and handling tylosin, use protective clothing and impervious gloves. If using a water medicating pump see table below, otherwise mix as follows:
To assure thorough dissolution, first place the contents of one jar in a mixing container and add one gallon of water (3785 mL) to the powder to make a concentrated solution. To make medicated drinking water containing 250 mg/gallon (66 ppm), mix this concentrated solution with water to make 400 gallons (1514 liters) of medicated drinking water. To make medicated drinking water containing 851 to 1,419 mg/gallon (225 to 375 ppm), mix this concentrated solution with water to make from 117 gallons + 51 ounces (444 liters) to 70 gallons + 64 ounces (267 liters) of medicated drinking water, respectively. To make medicated drinking water containing 2,000 mg/gallon (528 ppm), mix this concentrated solution with water to make 50 gallons (189 liters) of medicated drinking water.

Mixing Directions for Water Medicating Pump (1:128 inclusion)*:
Desired Concentration in Drinking water | Jars of Tylan Soluble | Volume of Water to Make Stock Solution
250 mg/gallon (66 ppm) | 1 | 3 gallons + 13 ounces
851 mg/gallon (225 ppm) | 5 | 4 gallons + 77 ounces
1,419 mg/gallon (375 ppm) | 9 | 5 gallons + 0 ounces
2,000 mg/gallon (528 ppm) | 10 | 3 gallons + 115 ounces
*This table applies only if the water medicating pump is set to deliver 1 ounce of stock solution per gallon of drinking water.

Mixing Directions for use in Honey Bees: Mix 200 mg tylosin in 20 g confectioners/powdered sugar. Use immediately.

Directions for Use

Chickens: NE indication: Administer medicated drinking water for a single five day period in broiler chickens. To assure all birds receive the intended medication, only medicated water should be available. These practices should be followed to assure both food safety and responsible antimicrobial drug use in chickens: 1) Use in flocks exhibiting signs of a necrotic enteritis outbreak, for example, increased mortality and lesions characteristic of necrotic enteritis upon necropsy; 2) Administer the full dose and dosing regimen once medication is initiated; 3) Use of Tylan Soluble or another macrolide is not advised if additional therapy is needed beyond the original course of medication. CRD indications: Administer medicated drinking water for three days; however, medicated water may be administered for one to five days depending upon severity of infection. Treated chickens must consume enough medicated water to provide 50 mg per pound of body weight per day. Only medicated water should be available to the birds.

Turkeys: Administer medicated drinking water for three days; however, medicated water may be administered for two to five days depending upon severity of infection. Treated turkeys must consume enough medicated water to provide 60 mg per pound of body weight per day. Only medicated water should be available to the birds.

Swine: SD indication: Administer medicated drinking water for 3 to 10 days, depending upon severity of infection. Alternatively, administer medicated drinking water for 3 to 10 days, followed by 40 to 100 g tylosin per ton of complete feed (Type C medicated feed manufactured from Tylan Type A medicated article) for 2 to 6 weeks. Only medicated water should be available to swine while medicating with Tylan Soluble. PPE indication: Administer medicated drinking water for 3 to 10 days, followed by 40 to 100 g of tylosin per ton of complete feed (Type C medicated feed manufactured from Tylan A medicated article) for 2 to 6 weeks. Only medicated water should be available to swine while medicating with Tylan Soluble.

Honey Bee Colonies: Administer three treatments of medicated confectioners sugar once weekly for 3 weeks. The 200 mg dose is applied (dusted) over the top bars of the brood chamber.

Warnings

User Safety Warnings: Not for Human Use. Keep Out of Reach of Children. Avoid contact with human skin. Exposure to tylosin may cause a rash.

Residue Warnings: Chickens must not be slaughtered for food within 24 hours after treatment. Do not use in layers producing eggs for human consumption.

Turkeys must not be slaughtered for food within five days after treatment.
Do not use in layers producing eggs for human consumption.

Swine must not be slaughtered for food within 48 hours after treatment.

Honey bees: The drug should be fed early in the spring or fall and consumed by the bees before the main honey flow begins, to avoid contamination of production honey. Complete treatments at least 4 weeks prior to main honey flow.

Manufactured For:
Elanco US, Inc. Store at or below 25°C (77°F)
Greenfield, IN 46140 U.S.A. Excursions Permitted to 40°C (104°F)
Product of the United Kingdom Avoid Moisture.

STORAGE AND HANDLING

To report suspected adverse events, for technical assistance or to obtain a copy of the Safety Data Sheet (SDS), contact Elanco US, Inc. at 1-888-545-5973.
For additional information about adverse drug experience reporting for animal drugs, contact FDA at 1-888-FDA-VETS or http://www.fda.gov/reportanimalae.

Tylan, Elanco and the diagonal bar logo are trademarks of Elanco or its affiliates.

© 2022 Elanco or its affiliates

Lot/Exp. date

47801-07

YL103717X

Principal Display Panel - Tylan Soluble Bottle Label

Elanco™

AF1300

Tylan™ Soluble
™

Tylosin Tartrate

Equivalent to 100 g (3.53 oz) tylosin base

CAUTION: Federal (USA) law restricts this drug to
use by or on the order of a licensed veterinarian.

For oral use in chickens, turkeys, swine, and honey bees.

Macrolide Antibiotic
Approved by FDA under NADA # 013-076

YL103717X